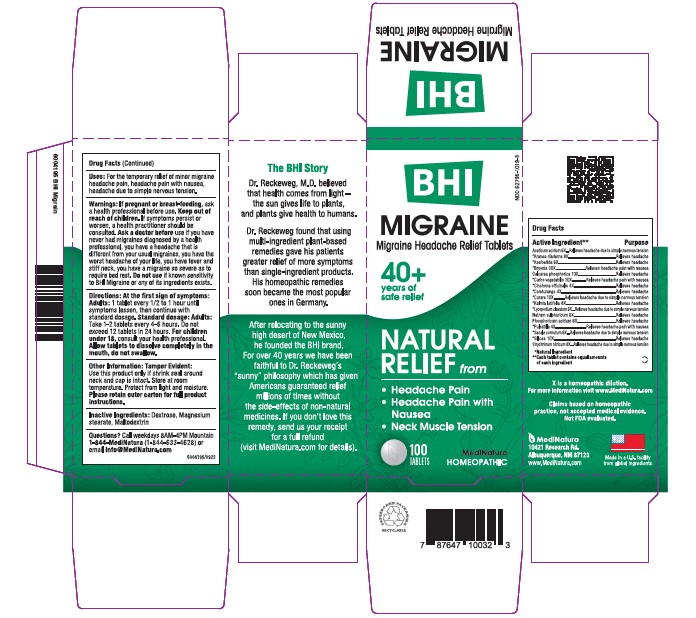 DRUG LABEL: BHI Migraine
NDC: 62795-1019 | Form: TABLET
Manufacturer: MediNatura Inc
Category: homeopathic | Type: HUMAN OTC DRUG LABEL
Date: 20230928

ACTIVE INGREDIENTS: ACETIC ACID 6 [hp_X]/1 1; ARANEUS DIADEMATUS 8 [hp_X]/1 1; ASAFETIDA 6 [hp_X]/1 1; BRYONIA ALBA WHOLE 30 [hp_X]/1 1; TRIBASIC CALCIUM PHOSPHATE 10 [hp_X]/1 1; ACTIVATED CHARCOAL 10 [hp_X]/1 1; CINCHONA OFFICINALIS BARK 4 [hp_X]/1 1; MARSDENIA CONDURANGO BARK 4 [hp_X]/1 1; TUBOCURARINE CHLORIDE 10 [hp_X]/1 1; KALMIA LATIFOLIA LEAF 8 [hp_X]/1 1; LYCOPODIUM CLAVATUM SPORE 6 [hp_X]/1 1; SODIUM SULFATE 6 [hp_X]/1 1; PHOSPHORIC ACID 6 [hp_X]/1 1; PULSATILLA VULGARIS 4 [hp_X]/1 1; CLAVICEPS PURPUREA SCLEROTIUM 6 [hp_X]/1 1; SILICON DIOXIDE 10 [hp_X]/1 1; STRYCHNINE NITRATE 8 [hp_X]/1 1
INACTIVE INGREDIENTS: MAGNESIUM STEARATE; MALTODEXTRIN; DEXTROSE

BHI Migraine Tablet

INGREDIENT SECTIONS

Each tablet contains: Aceticum acidum 6X, *Aranea diadema 8X, *Asafoetida 6X, *Bryonia alba 30X, Calcarea phosphorica 10X, *Carbo vegetabilis 10X, *Cinchona officinalis 4X, *Condurango 4X, *Curare 10X, *Kalmia latifolia 8X, *Lycopodium clavatum 6X, Natrum sulphuricum 6X, Phosphoricum acidum 6X, *Pulsatilla 4X, *Secale cornutum 6X, *Silicea 10X, Strychninum nitricum 8X 17.6 mg each.

*Natural Ingredients

INACTIVE INGREDIENTS

Inactive Ingredients: Dextrose, Magnesium Stearate, Maltodextrin

PURPOSE

Migraine Relief Tablets

Relieves:

• Headache Pain

• Headache Pain with Nausea

• Neck Muscle Tension

USES

For the temporary relief of minor migraine headache pain, headache pain with nausea, headache due to simple nervous tension

DIRECTIONS

At first sign of symptoms:
Adults: 1 tablet every 1/2 to 1 hour until symptoms lessen, then continue with standard dosage.
Standard dosage: Adults: Take 1-2 tablets every 4 to 6 hours. Do not exceed 12 tablets in 24 hours. For children under 18, consult your health professional. Allow tablets to dissolve completely in the mouth, do not swallow.

WARNINGS

If pregnant or breast-feeding, ask a health professional before use. Keep out of reach of children. If symptoms persist or worsen, a health professional should be consulted. Ask a doctor before use if you have never had migraines diagnosed by a health professional, you have a headache that is different from your usual migraines, you have the worst headache of your life, you have fever and stiff neck, you have a migraine so severe as to require bed rest. Do not use if known sensitivity to BHI Migraine or any of its ingredients exists.

KEEP OUT OF REACH OF CHILDREN

PACKAGE LABEL

Add image transcription here...